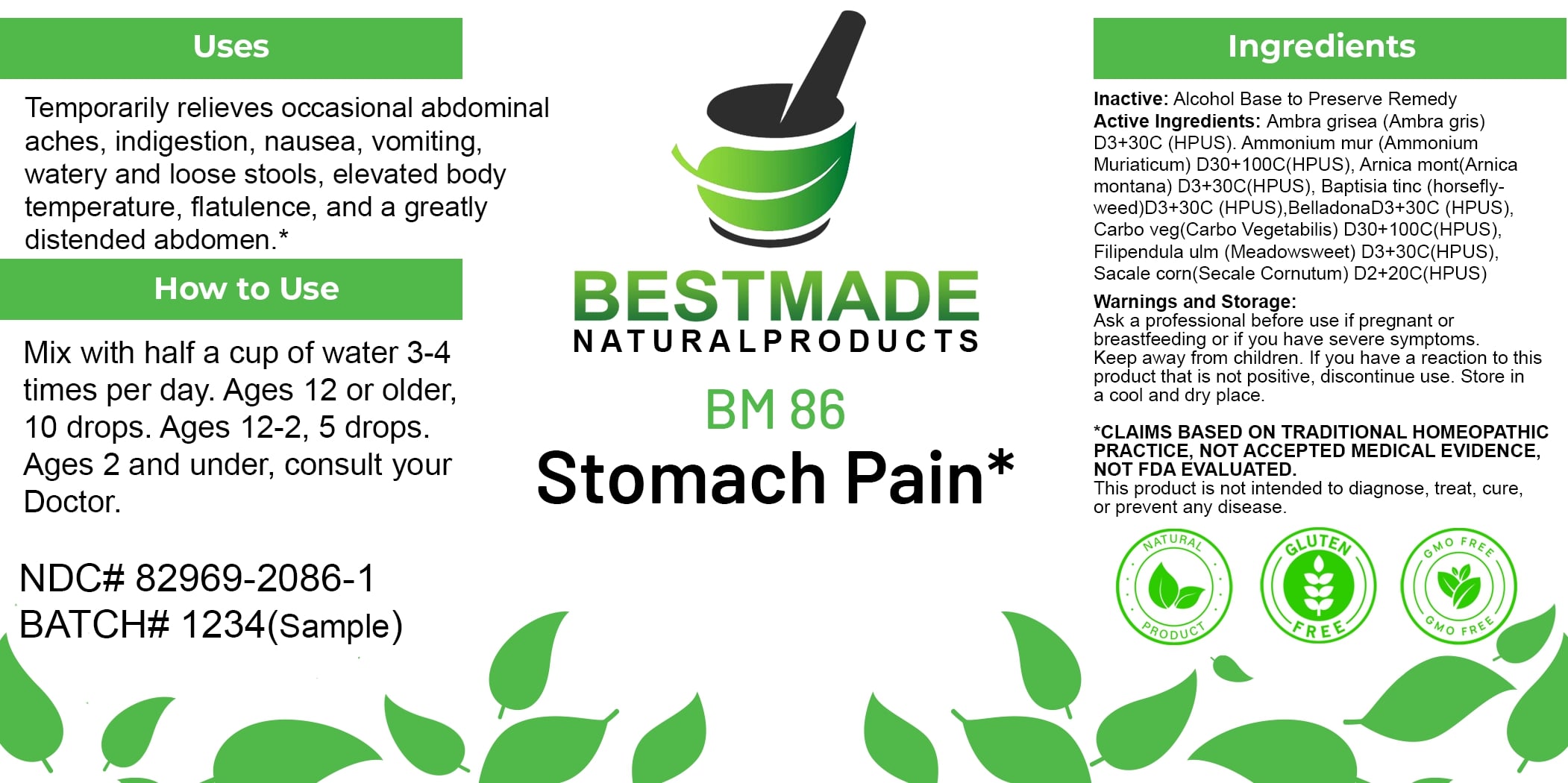 DRUG LABEL: Bestmade Natural Products BM86
NDC: 82969-2086 | Form: LIQUID
Manufacturer: Bestmade Natural Products
Category: homeopathic | Type: HUMAN OTC DRUG LABEL
Date: 20250203

ACTIVE INGREDIENTS: ARNICA MONTANA 30 [hp_C]/30 [hp_C]; ATROPA BELLADONNA 30 [hp_C]/30 [hp_C]; ACTIVATED CHARCOAL 30 [hp_C]/30 [hp_C]; AMMONIUM CHLORIDE 30 [hp_C]/30 [hp_C]; BAPTISIA TINCTORIA ROOT 30 [hp_C]/30 [hp_C]; CLAVICEPS PURPUREA SCLEROTIUM 30 [hp_C]/30 [hp_C]; AMBERGRIS 30 [hp_C]/30 [hp_C]; FILIPENDULA ULMARIA ROOT 30 [hp_C]/30 [hp_C]
INACTIVE INGREDIENTS: ALCOHOL 30 [hp_C]/30 [hp_C]

BM86

DOSAGE AND ADMINISTRATION

How to Use

Mix with half a cup of water 3-4 times per day. Ages 12 or older, 10 drops. Ages 12-2, 5 drops. Ages 2 and under, consult your Doctor.

INACTIVE INGREDIENT

Ingredients

Inactive: Alcohol Base to Preserve Remedy

ACTIVE INGREDIENT

Active Ingredients: Ambra grisea (Ambra gris) D3+30C (HPUS), Ammonium mur (Ammonium muriaticum) D30+100C (HPUS), Arnica mont(Arnica montana) D3+30C (HPUS), Baptisia tinc (horsfly-weed)D3+30C (HPUS), BelladonnaD3+30C (HPUS), Carbo veg(Carbo Vegetabilis) D30+100C (HPUS), Filipendula ulm (Meadowsweet) D3+30C (HPUS), Sacale corn(Secale Cornutum) D2+20C (HPUS)

Uses

Temporarily relieves occasional abdominal aches, indigestion, nausea, vomiting, watery and loose stools, elevated body temperature, flatulence, and a greatly distended abdomen.*

*CLAIMS BASED ON TRADITIONAL HOMEOPATHIC PRACTICE, NOT ACCEPTED MEDICAL EVIDENCE, NOT FDA EVALUATED.

This product is not intended to diagnose, treat, cure, or prevent any disease.

Uses

Temporarily relieves occasional abdominal aches, indigestion, nausea, vomiting, watery and loose stools, elevated body temperature, flatulence, and a greatly distended abdomen.*

*CLAIMS BASED ON TRADITIONAL HOMEOPATHIC PRACTICE, NOT ACCEPTED MEDICAL EVIDENCE, NOT FDA EVALUATED.

This product is not intended to diagnose, treat, cure, or prevent any disease.

KEEP OUT OF REACH OF CHILDREN

Warnings and Storage:

Ask a professional before use if pregnant or breastfeeding or if you have severe symptoms. Keep away from children. If you have a reaction to this product that is not positive, discontinue use. Store in a cool and dry place.

Warnings and Storage:

Ask a professional before use if pregnant or breastfeeding or if you have severe symptoms. Keep away from children. If you have a reaction to this product that is not positive, discontinue use. Store in a cool and dry place.

*CLAIMS BASED ON TRADITIONAL HOMEOPATHIC PRACTICE, NOT ACCEPTED MEDICAL EVIDENCE, NOT FDA EVALUATED.

This product is not intended to diagnose, treat, cure, or prevent any disease.

Entire package label